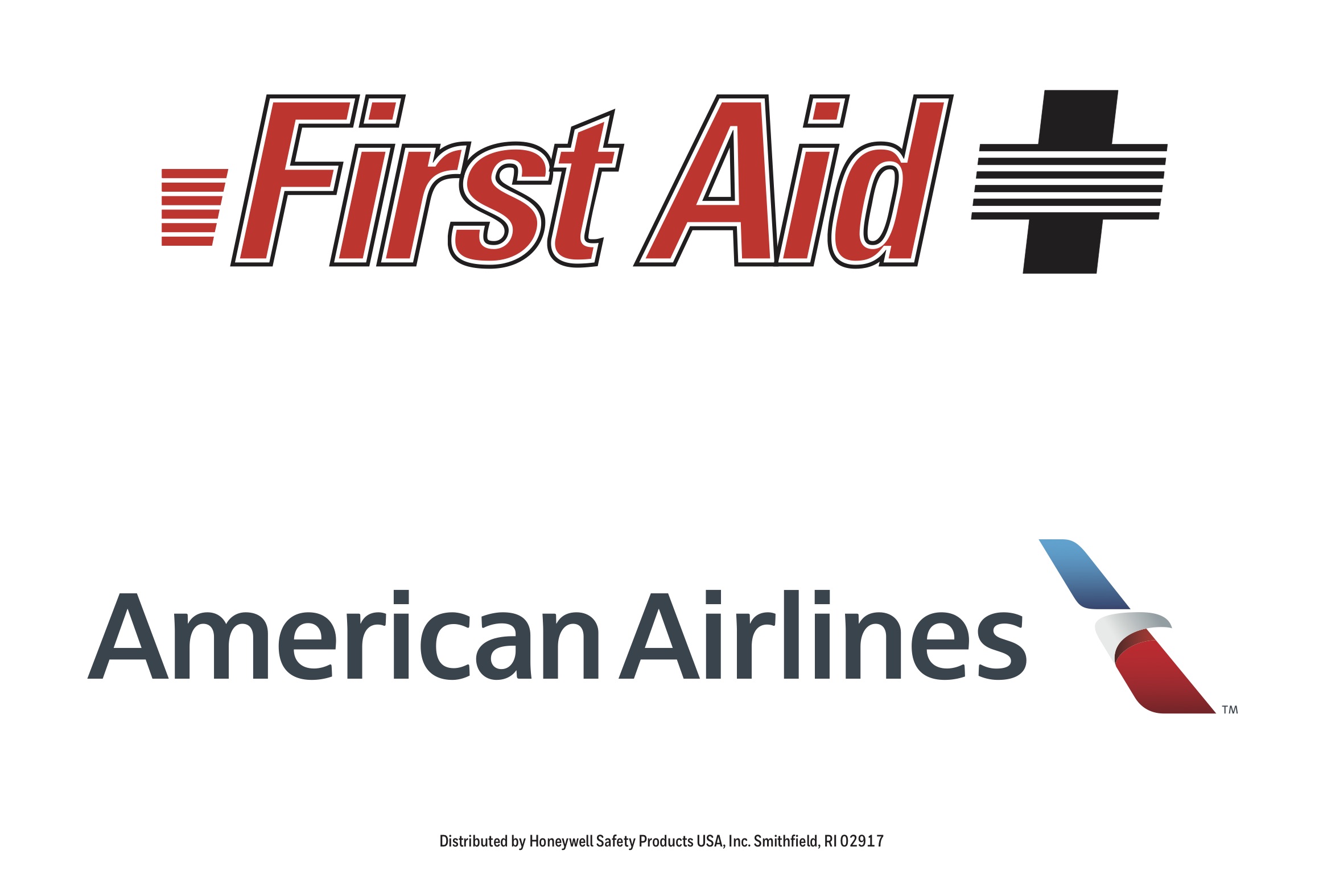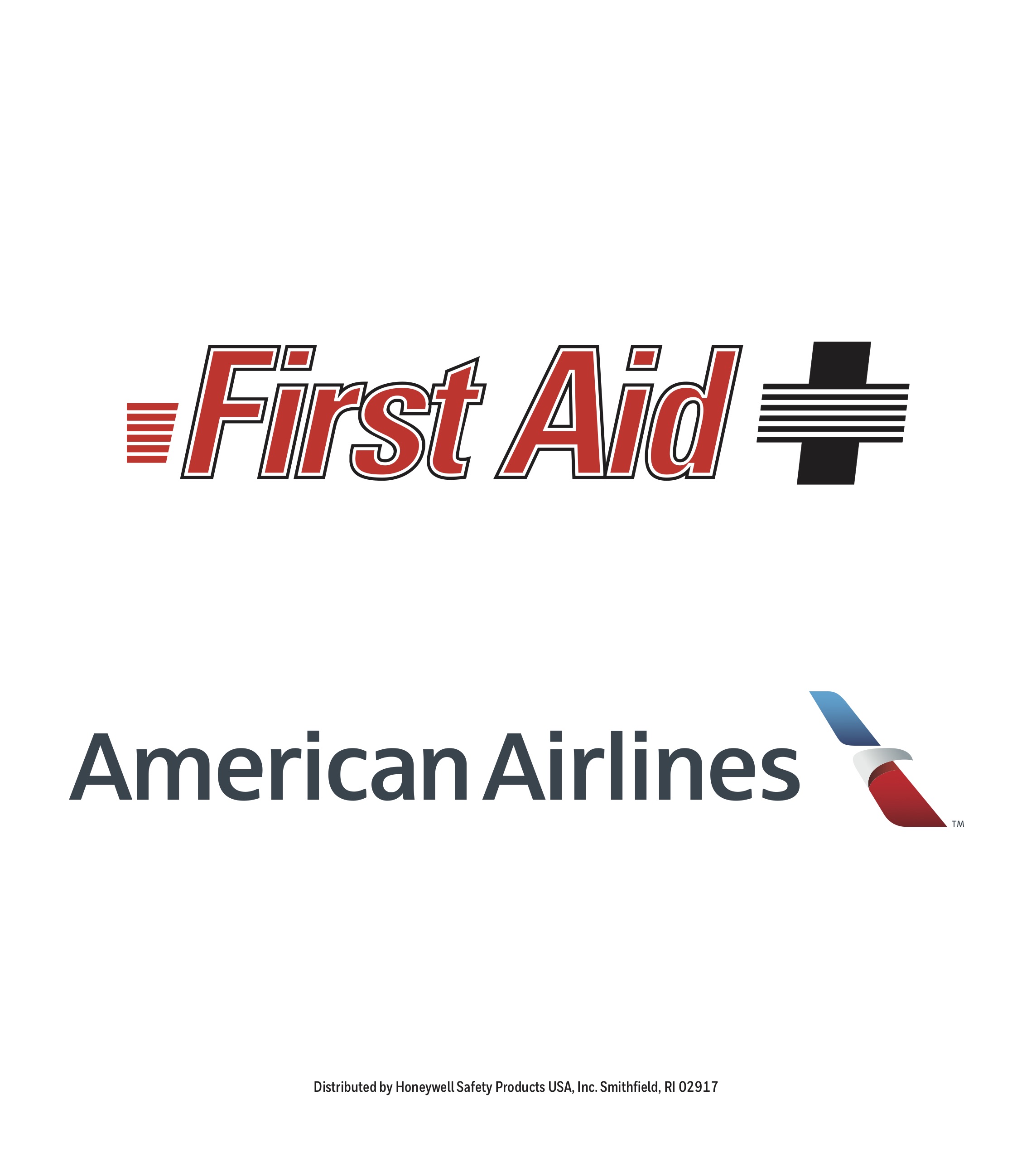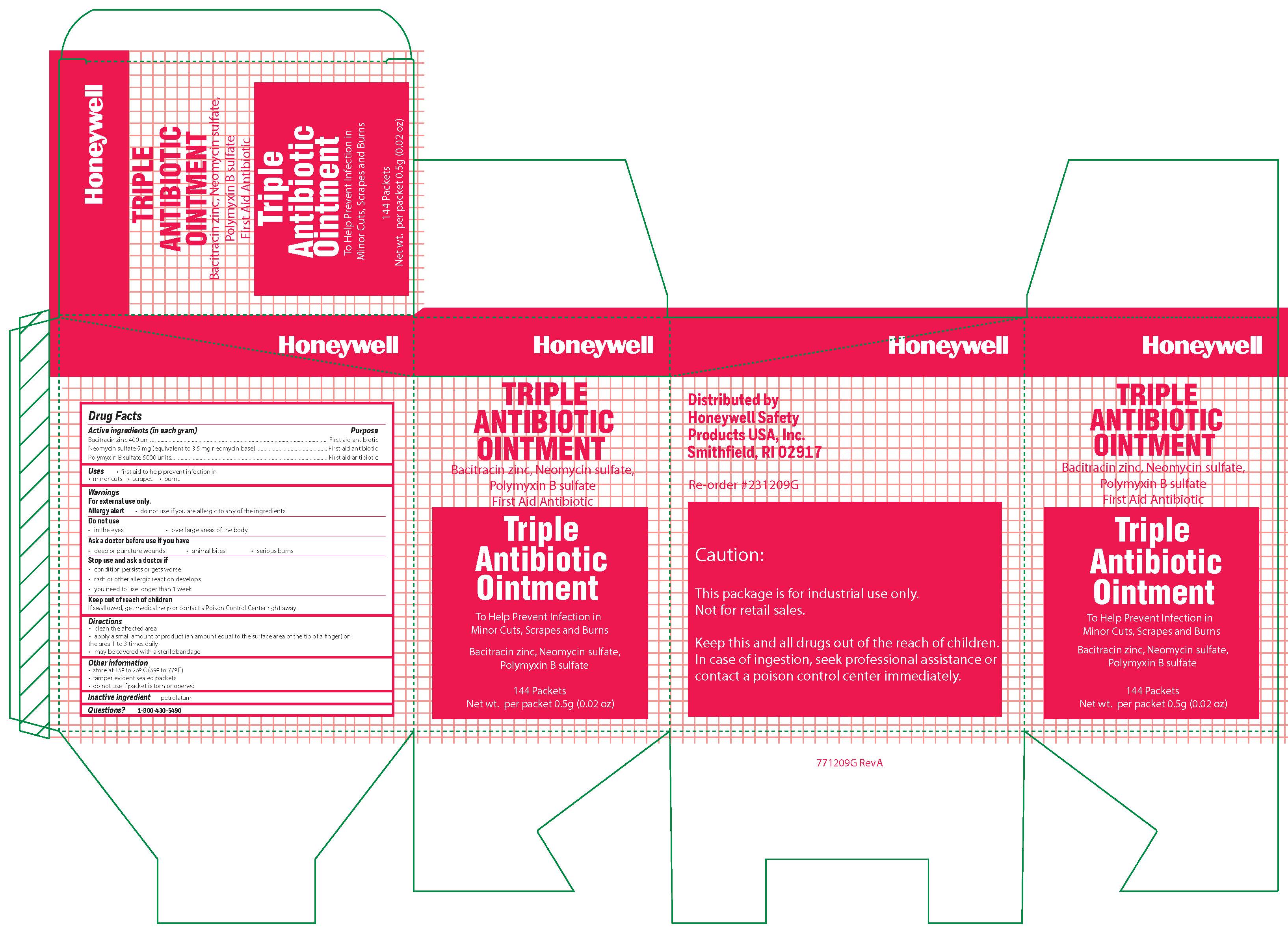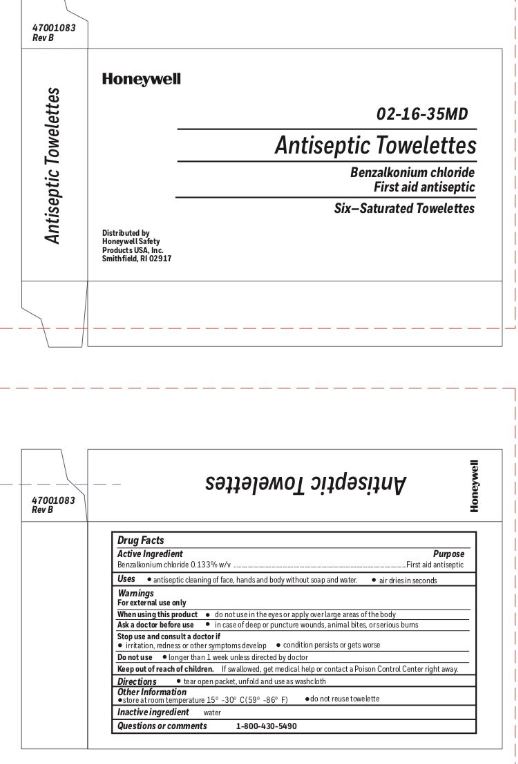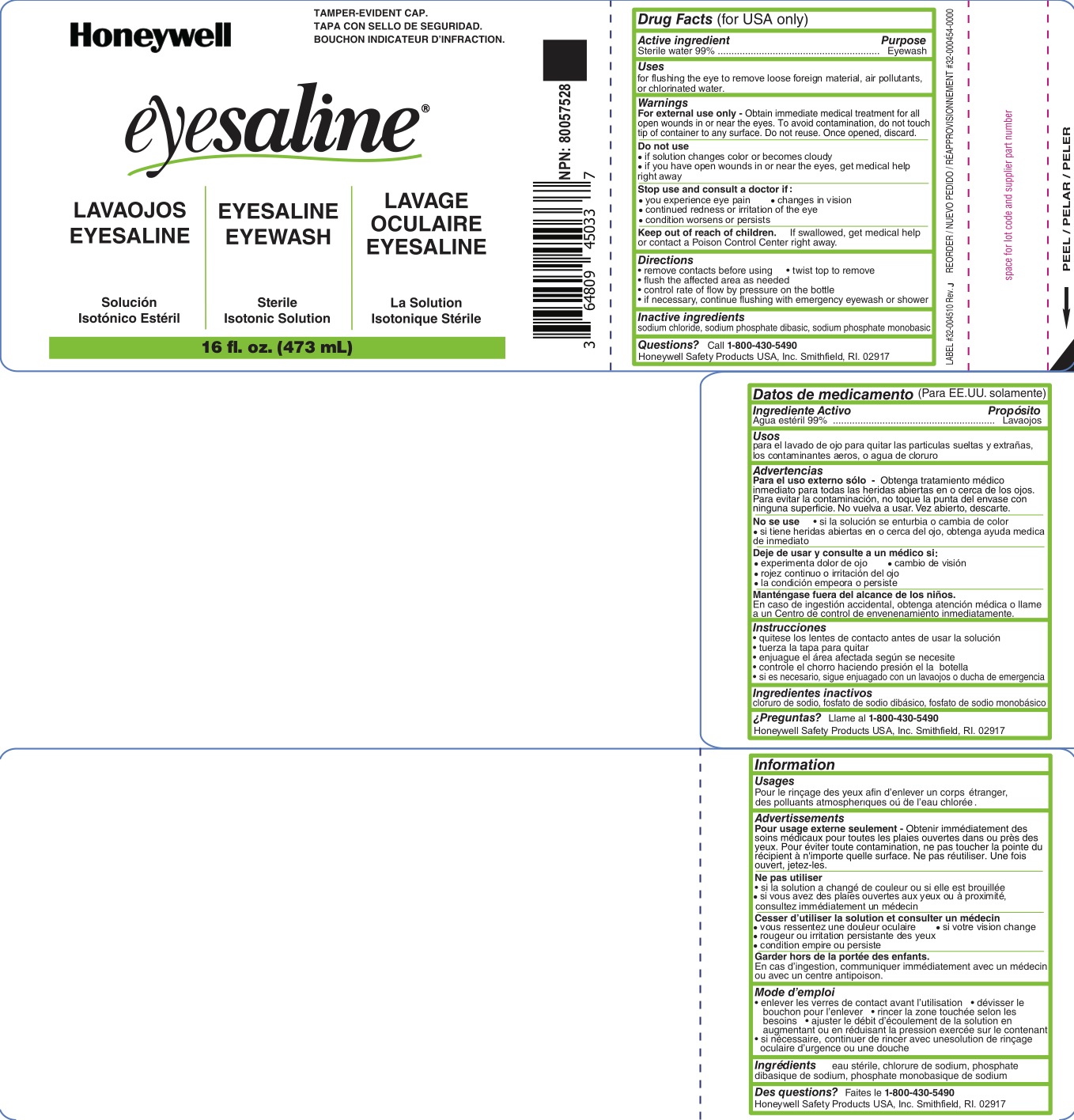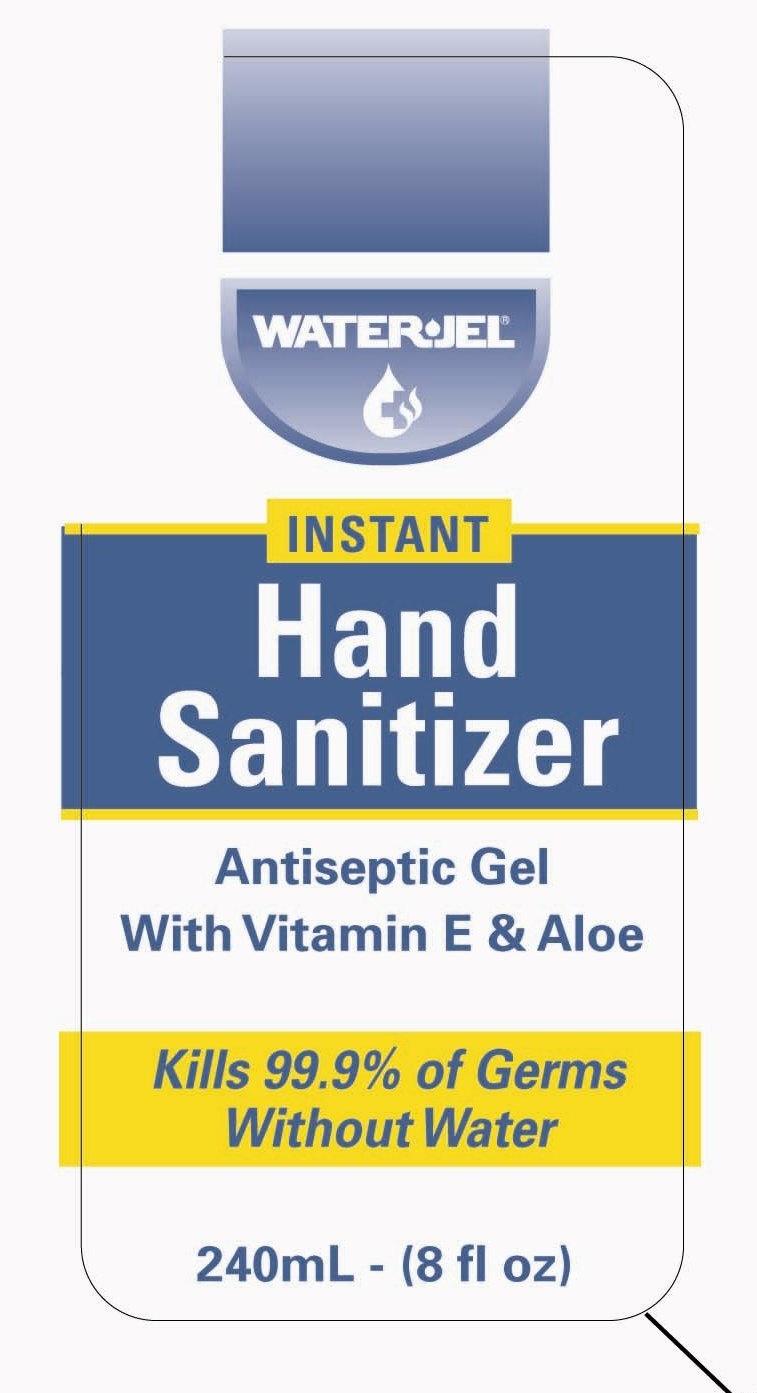 DRUG LABEL: 4314 First Aid Kit
NDC: 0498-4314 | Form: KIT | Route: OPHTHALMIC
Manufacturer: Honeywell Safety Products USA, Inc.
Category: otc | Type: HUMAN OTC DRUG LABEL
Date: 20190510

ACTIVE INGREDIENTS: WATER 98.6 mL/100 mL; POLYMYXIN B SULFATE 5000 [iU]/1 g; BACITRACIN ZINC 400 [iU]/1 g; NEOMYCIN SULFATE 3.5 mg/1 g; BENZALKONIUM CHLORIDE 1.3 mg/1 mL; ALCOHOL 62 mL/100 mL
INACTIVE INGREDIENTS: SODIUM PHOSPHATE, DIBASIC; SODIUM PHOSPHATE, MONOBASIC, MONOHYDRATE; SODIUM CHLORIDE; PETROLATUM; WATER; ALOE VERA LEAF; PROPYLENE GLYCOL; .ALPHA.-TOCOPHEROL ACETATE, DL-; TRIISOPROPANOLAMINE; CARBOMER COPOLYMER TYPE A; WATER

4314, 4315 First Aid Kit (Triple, EW, BZK wipe, antiseptic hand gel- SF00004528, SF00004529)

Triple Active ingredient

Bacitracin zinc 400 units

Neomycin sulfate (5 mg equivalent to 3.5 mg Neomycin base)

Polymyxin B sulfate 5000 units

Triple Purpose

First aid antibiotic

First aid antibiotic

First aid antibiotic

Triple Uses

first aid to help prevent infection in:

- minor cuts
- scrapes
- burns

Triple Warnings

For external use only

Allergy alert: do not use if you are allergic to any of the ingredients

Do not use

- in the eyes
- over large areas of the body
- Ask a doctor before use if you have
- a deep or puncture wounds
- animal bites
- serious burns

Stop use and ask a doctor if

- the condition persists or gets worse
- a rash or other allergic reaction develops
- you need to use longer than 1 week

Keep out of the reach of children

If swallowed, get medical help or contact a Poison Control Center right away.

Triple Directions

- clean the affected area
- apply a small amount of the product (an amount equal to the surface area of the tip of a finger) on the area 1 to 3 times daily
- may be covered with a sterile bandage

Triple Other information

- store at 15^0 to 25^0 C (59^0 to 77^0 F)
- tamper evident sealed packets
- do not use if packet is torn or opened

Triple Inactive ingredient

petrolatum

Triple Questions?

1-800-430-5490

BZK Wipe Active ingredient

Benzalkonium chloride 0.13% w/v

BZK Wipe Purpose

First aid antiseptic

BzK Wipe Uses

Antiseptic cleansing of face, hands, and body without soap and water

BZK Wipe Warnings

For external use only

Do not use

- in the eyes or over large areas of the body
- on mucous membranes
- on irritated skin
- in case of deep puncture wounds, animal bites or serious burns, consult a doctor
- longer than 1 week unless directed by a doctor

Stop use and ask a doctor if

- if irritation, redness or other symptoms develop
- the condition persists or gets worse

Keep out of reach of children

If swallowed, get medical help or contact a Poison Control Center right away.

BZK Wipe Directions

tear open packet and use as a washcloth

BZK Wipe Other information

- store at room temperature 15^0 to 30^0 C (59^0 - 86^0 F)
- do not reuse towelette

BZK Wipe Inactive ingredient

water

BZK Wipe Questions

1-800-430-5490

Eyewash Active ingredient

Sterile Water 99%

Eyewassh Purpose

Eyewash

Eyewash Uses

- for flushing the eye to remove loose foreign material, air pollutants or chlorinated water

Eyewash Warnings

For external use only

- Obtain immediate medical treatment for all open wounds in or near eyes.
- To avoid contamination, do not touch tip of container to any surface.
- Do not reuse.
- Once opened, discard.

Do not use

- if solution changes color or becomes cloudy
- if you have open wounds in or near the eyes, get medical help right away.

Stop use and ask a doctor if

- you experience eye pain
- changes in vision
- continued redness or irritation of the eye
- condition worsens or persists

Keep out of reach of children

If swallowed, get medical help or contact a Poison Control Center right away.

Eyeash Directions

- remove contacts before using
- twist top to remove
- flush the affected area as needed
- control rate of flow by pressure on the bottle
- if necessary, continue flushing with emergency eyewash or shower

Eyewash Inactive ingredients

sodium chloride, sodium phosphate dibasic, sodium phosphate monobasic

Eyeash Questions

Call 1-800-430-5490 Honeywell Safety Products USA, Inc. Smithfield, RI 02917

Hand Sanitizer Active ingredient

Ethyl alcohol 62%

Hand Sanitizer Purpose

Antiseptic handwash

Hand Sanitizer Uses

- for hand washing to decrease bacteria on skin
- recommended for repeated use

Hand Sanitizer Warnings

For external use only

Flammable, keep away from fire or flame

When using this product

- do not use in the eyes
- discontinue use if irritation and redness develops. If condition persists for more than 72 hours consult a doctor.

Keep out of reach of children

If swallowed, get medical help or contact a Poison Control Center right away.

Hand Sanitizer Directions

wet hands thoroughly with product and allow to dry without wiping

Hand Sanitizer Other information

- store at 15^0 to 25^0 C (59^0 to 77^0 F)

Hand Sanitizer Inactive ingredients

acrylates/C10-30 alkyl acrylate crosspolymer, aloe barbadensis leaf juice, dl-alpha tocopheryl acetate, fragrance, PEG-60 almond glycerides, propylene glycol, purified water, triisopropanolamine

Hand Sanitizer Questions or Comments?

1-800-275-3433 info@waterjel.com www.waterjel.com

4314 Sf00004528 Kit Contents

1 1X3 PLASTIC 100/BOX

1 TRIPLE ANTIBIOTIC 10 PER

1 EYE DRESS PKT W/4 ADH STRIPS

1 TRIANGULAR BDG, NON-STERILE

2 GAUZE PADS, 3" X 3", 4 PER

1 GAUZE BANDAGE, 2" X 6 YD,2 PER

1 INSTANT COLD PACK 4" X 6"

1 BUFFERED EYE WASH 1 OZ BTL

1 WATER JEL DRESSING 4" X 4"

2 TOPICAL COOLING JEL

1 NITRILE GLOVES 2PR BBP

1 ANTIMCRBL ANTSPTC TWLETTS

1 ADHES TAPE W/P 1"X 2 1/2 YD

1 1FIRST AID GUIDE ASHIEMERGENCY SURVIVAL BLANKET

1 HAND SANITIZER 0.9G WJ 25/BX

2 BLOODSTOPPER

1 CPR FILTERSHIELD 77-100

1 F A KIT EMPTY BLANK 140

1 LBL STOCK 6-3/8"X4"

1 LBL STOCK 4"X2-7/8"

1 SCISSORS ANGLED 1EA IN BAG

4315 SF00004529 kit contents

1 1X3 PLASTIC 100/BOX

3 TRIPLE ANTIBIOTIC 10 PER

1 EYE DRESS PKT W/4 ADH STRIPS

1 GAUZE BANDAGE, 4" X 6 YD

1 TOURNIQUET AND FORCEPS 1 EA

2 TRIANGULAR BDG, NON-STERILE

4 GAUZE PADS, 3" X 3", 4 PER

2 GAUZE BANDAGE, 2" X 6 YD,2 PER

2 INSTANT COLD PACK 4" X 6"

2 WATER JEL DRESSING 4" X 4"

5 TOPICAL COOLING JEL

2 NITRILE GLOVES 2PR BBP

5 ANTIMCRBL ANTSPTC TWLETTS

2 ADHES TAPE W/P 1"X 2 1/2 YD

1 FIRST AID GUIDE ASHI

1 EMERGENCY SURVIVAL BLANKET

1 HAND SANITIZER 0.9G WJ 25/BX

4 BLOODSTOPPER

1 CPR FILTERSHIELD 77-100

1 4OZ BFS EYEWASH TRILINGUAL BOTTLE

1 180 EMPTY BLANK NO LOGO

1 SAM SPLINT 4.5"X36" ORNGE/BL

1 LBL STOCK 6-3/8"X4"

1 LBL STOCK 4"X2-7/8"

1 SCISSORS ANGLED 1EA IN BAG